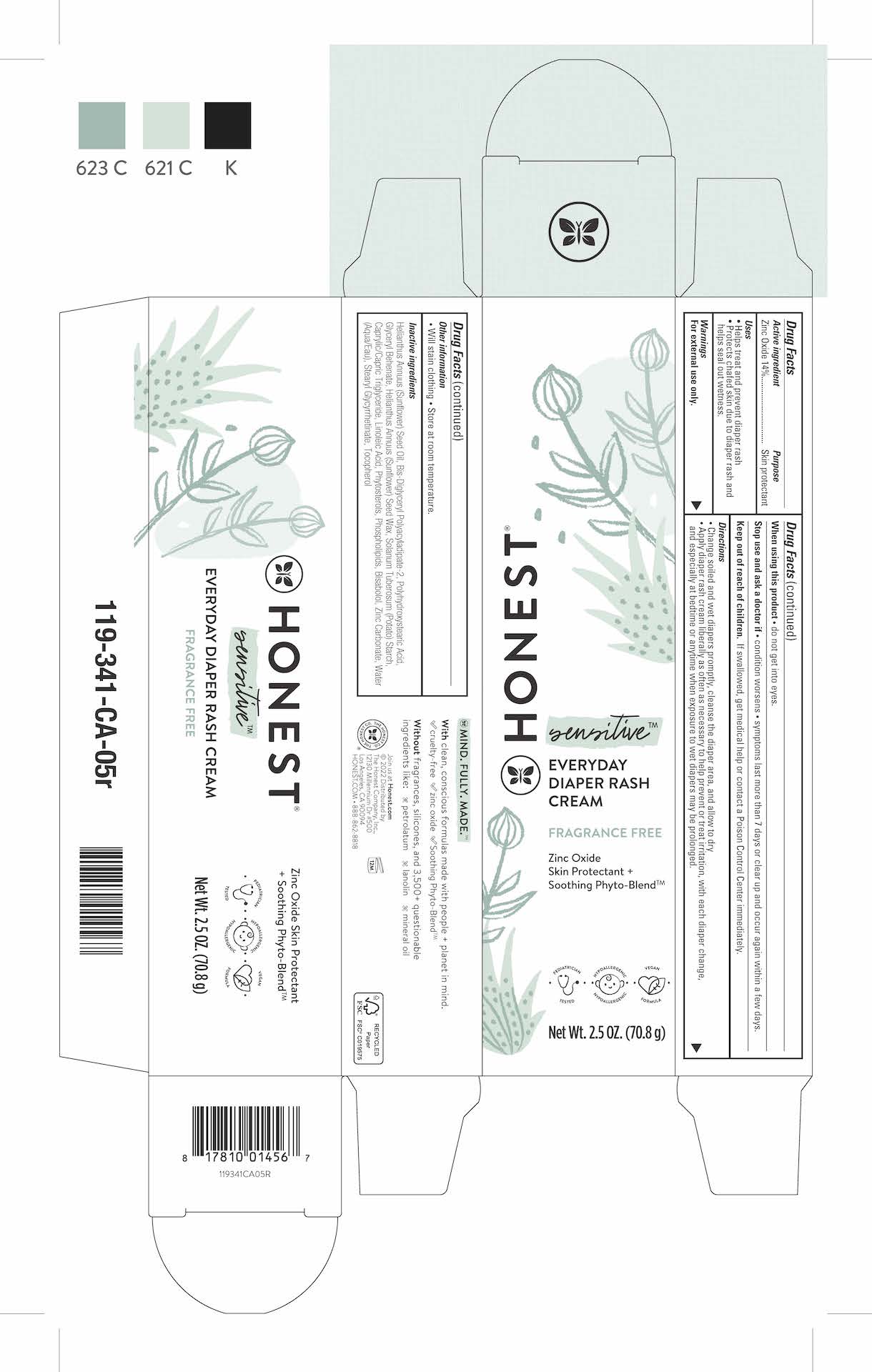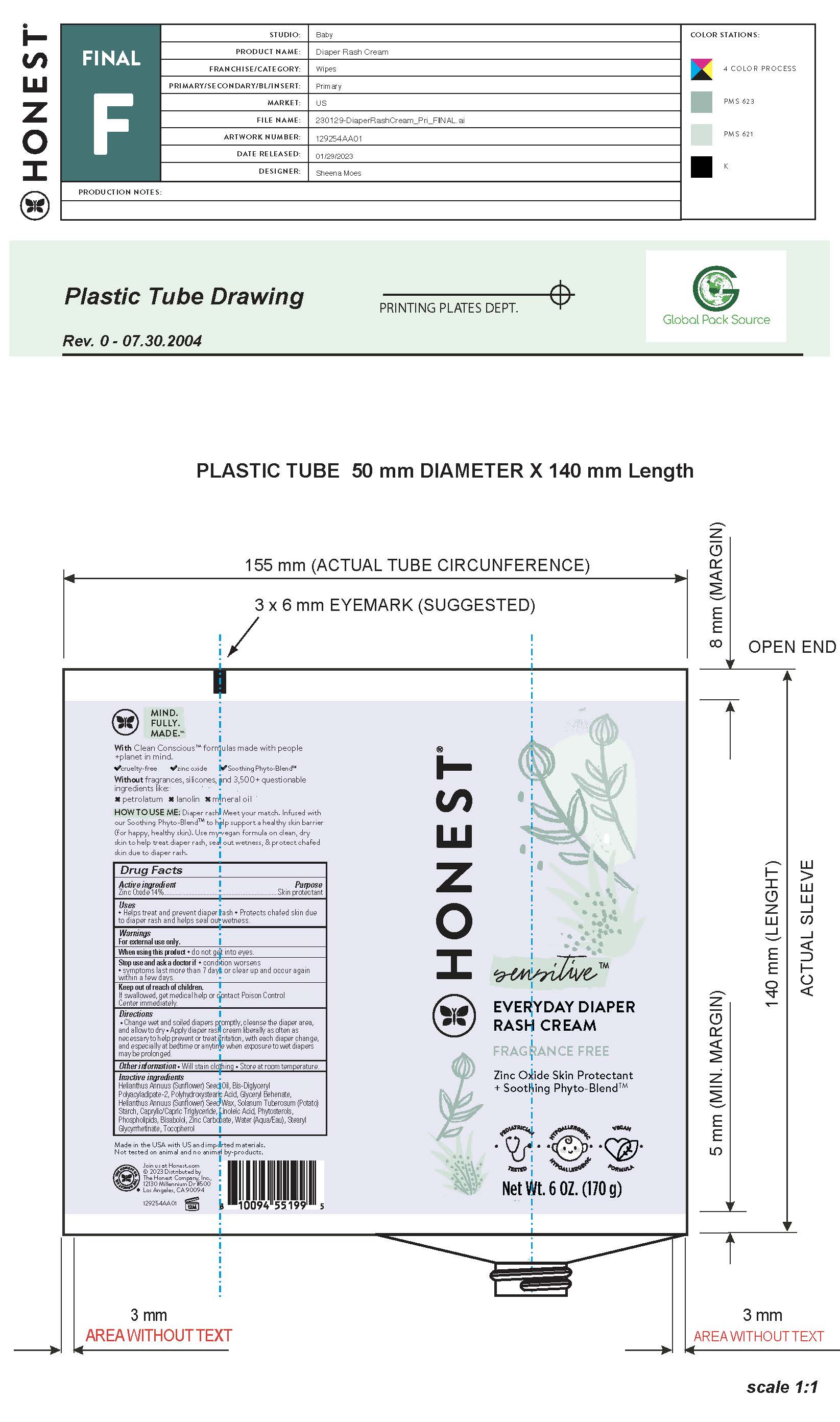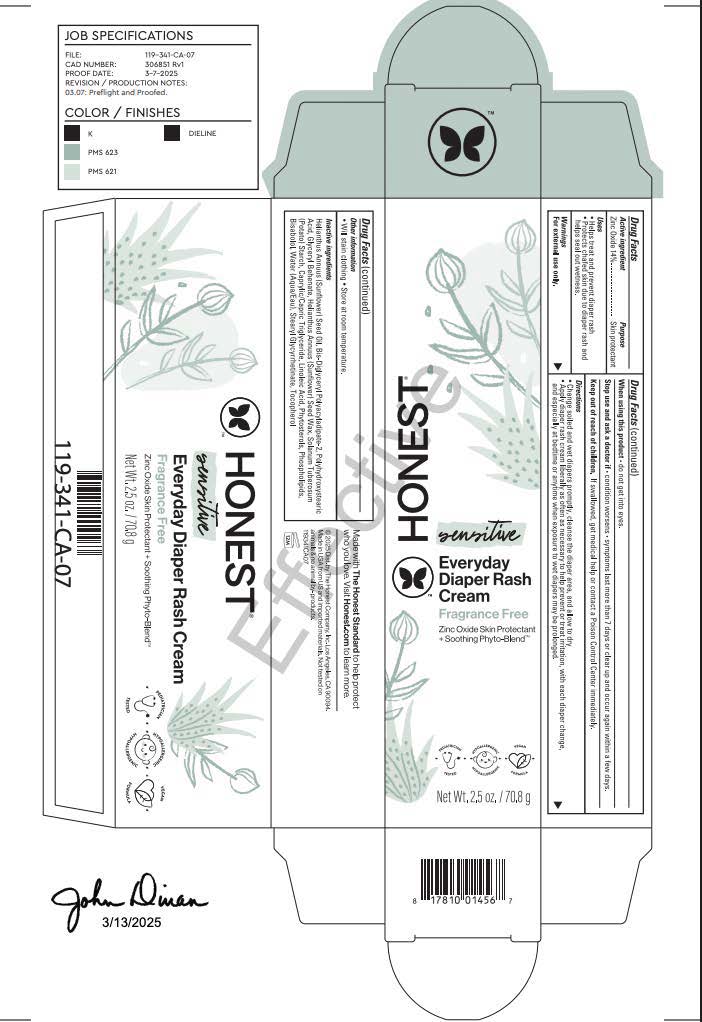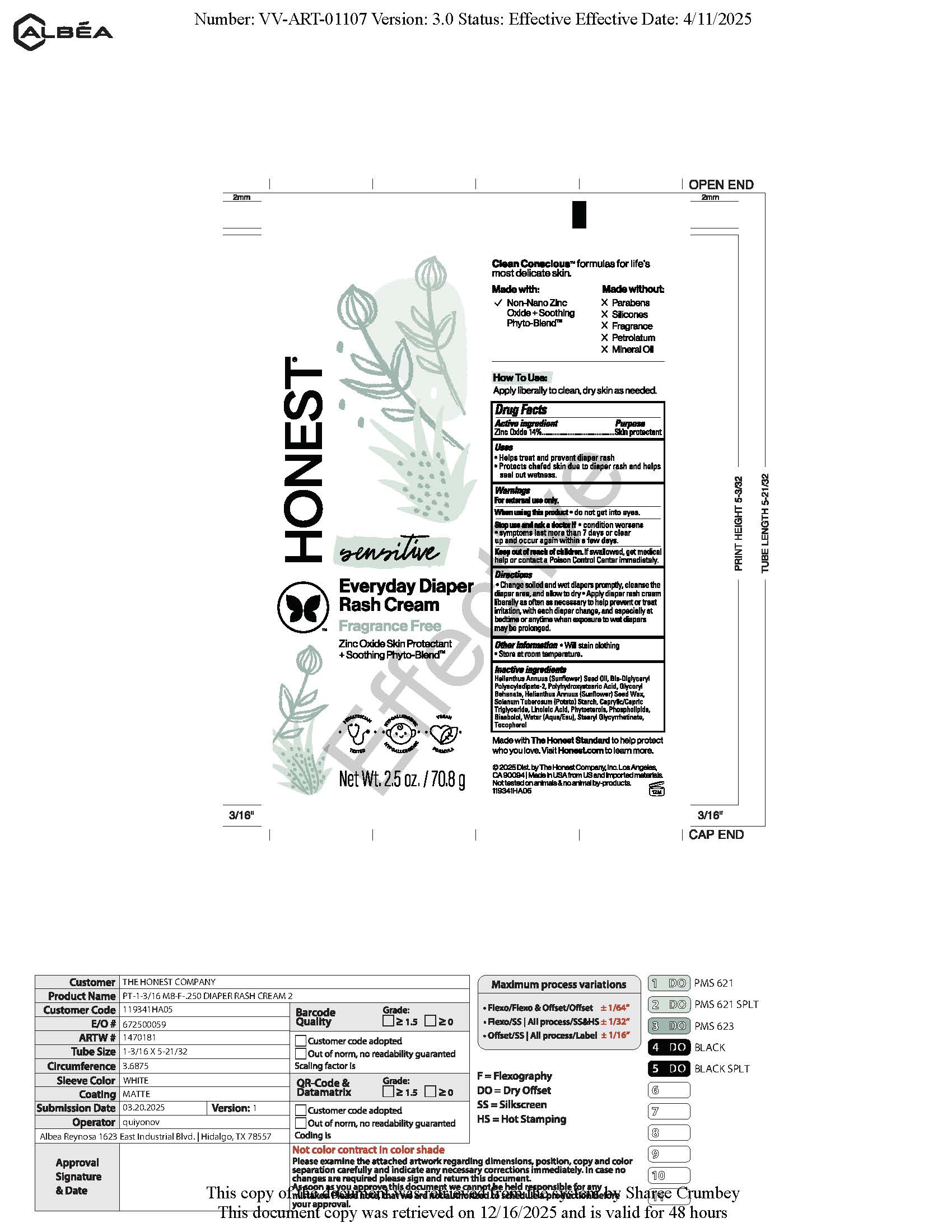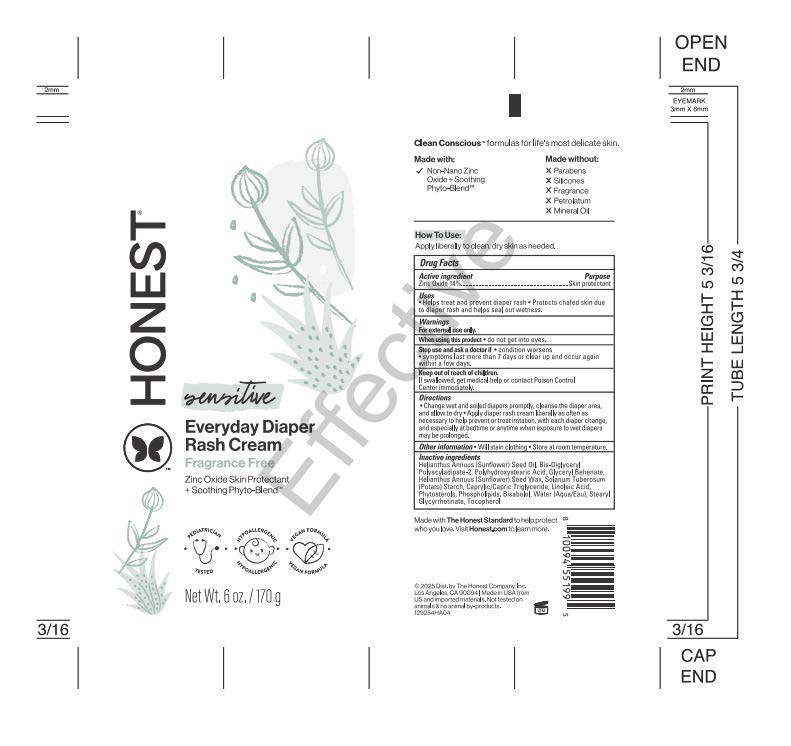 DRUG LABEL: Everyday Diaper Rash Cream
NDC: 69366-507 | Form: CREAM
Manufacturer: The Honest Company, Inc
Category: otc | Type: HUMAN OTC DRUG LABEL
Date: 20251216

ACTIVE INGREDIENTS: ZINC OXIDE 14 g/100 g
INACTIVE INGREDIENTS: TOCOPHEROL; POLYHYDROXYSTEARIC ACID (2300 MW); STEARYL GLYCYRRHETINATE; LEVOMENOL; BIS-DIGLYCERYL POLYACYLADIPATE-2; HELIANTHUS ANNUUS SEED WAX; STARCH, POTATO; WATER; GLYCERYL DIBEHENATE; MEDIUM-CHAIN TRIGLYCERIDES; LINOLEIC ACID; SOY STEROL; LECITHIN, SOYBEAN; SUNFLOWER OIL

Everyday Diaper Rash Cream

Active ingredient

Zinc Oxide 14%

Purpose

Skin protectant

Uses:

- Helps treat and prevent diaper rash
- Protects chafed skin due to diaper rash and helps seal out wetness.

Warnings:
For external use only.

When using this product • do not get into eyes.

Stop use and ask a doctor if • condition worsens • symptoms last more than 7 days or clear up and occur again within a few days.

Keep out of reach of children. If swallowed, get medical help or contact a Poison Control Center immediately.

Directions:

- Change soiled and wet diapers promptly, cleanse the diaper area, and allow to dry
- Apply diaper rash cream liberally as often as necessary to help prevent or treat irritation, with each diaper change, and especially at bedtime or anytime when exposure to wet diapers may be prolonged.

Other information:
• Will stain clothing • Store at room temperature.

Inactive ingredients:
Helianthus Annuus (Sunflower) Seed Oil, Bis-Diglyceryl Polyacyladipate-2, Polyhydroxystearic Acid,
Glyceryl Behenate, Helianthus Annuus (Sunflower) Seed Wax, Solanum Tuberosum (Potato) Starch,
Caprylic/Capric Triglyceride, Linoleic Acid, Phytosterols, Phospholipids, Bisabolol, Zinc Carbonate,Water
(Aqua/Eau), Stearyl Glycyrrhetinate, Tocopherol

Inactive ingredients:
Helianthus Annuus (Sunflower) Seed Oil, Bis-Diglyceryl Polyacyladipate-2, Polyhydroxystearic Acid,
Glyceryl Behenate, Helianthus Annuus (Sunflower) Seed Wax, Solanum Tuberosum (Potato) Starch,
Caprylic/Capric Triglyceride, Linoleic Acid, Phytosterols, Phospholipids, Bisabolol, Water
(Aqua/Eau), Stearyl Glycyrrhetinate, Tocopherol

PACKAGE LABEL

HONEST®

EVERYDAY DIAPER RASH CREAM

FRAGRANCE FREE

Zinc Oxide

Skin Protectant +

Soothing Phyto-Blend™

Net Wt. 2.5 oz. (70.8 g)

© 2022 Distributed by
The Honest Company, Inc.,
12130 Millennium Dr #500
Los Angeles, CA 90094
HONEST.COM • 888-862-8818

PACKAGE LABEL

HONEST ®

EVERYDAY DIAPER RASH CREAM

FRAGRANCE FREE

Zinc Oxide

Skin Protectant +

Soothing Phyto-Blend™

Net Wt. 2.5 oz. (70.8 g)

© 2022 Distributed by

The Honest Company, Inc.,

12130 Millennium Dr #500

Los Angeles, CA 90094

HONEST.COM